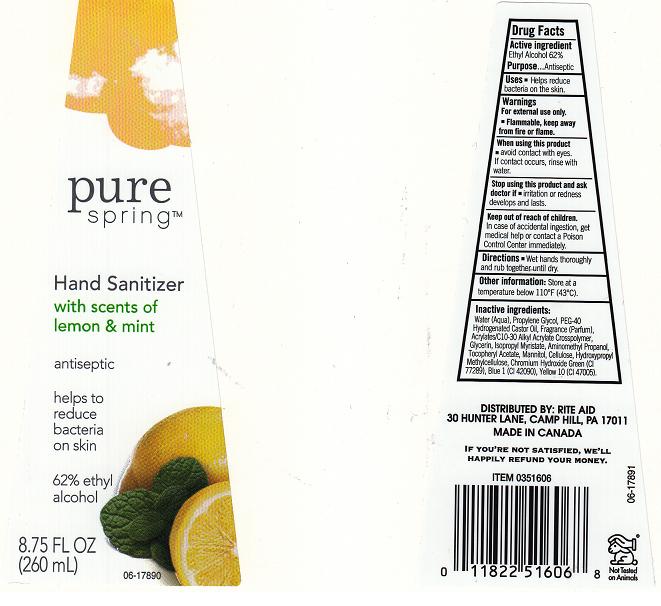 DRUG LABEL: PURE SPRING
NDC: 11822-4670 | Form: LIQUID
Manufacturer: RITE AID CORPORATION
Category: otc | Type: HUMAN OTC DRUG LABEL
Date: 20120319

ACTIVE INGREDIENTS: ALCOHOL 62 mL/100 mL
INACTIVE INGREDIENTS: WATER; PROPYLENE GLYCOL; POLYOXYL 40 HYDROGENATED CASTOR OIL; CARBOMER COPOLYMER TYPE A; GLYCERIN; ISOPROPYL MYRISTATE; AMINOMETHYLPROPANOL; .ALPHA.-TOCOPHEROL ACETATE; MANNITOL; .ALPHA.-CELLULOSE; HYPROMELLOSE 2208 (100 MPA.S); CHROMIC OXIDE; FD&C BLUE NO. 1; D&C YELLOW NO. 10

DRUG FACTS

ACTIVE INGREDIENT

ETHYL ALCOHOL 62%

PURPOSE

ANTISEPTIC

USES

HELPS REDUCE BACTERIA ON THE SKIN

WARNINGS

FOR EXTERNAL USE ONLY. FLAMMABLE, KEEP AWAY FROM FIRE OR FLAME.

WHEN USING THIS PRODUCT

AVOID CONTACT WITH EYES. IF CONTACT OCCURS, RINSE WITH WATER.

STOP USING THIS PRODUCT AND ASK DOCTOR IF

IRRITATION OR REDNESS DEVELOPS AND LASTS.

KEEP OUT OF REACH OF CHILDREN

IN CASE OF ACCIDENTAL INGESTION, GET MEDICAL HELP OR CONTACT POISON CONTROL CENTER IMMEDIATELY.

DIRECTIONS

WET HANDS THOROUGHLY AND RUB TOGETHER UNTIL DRY.

OTHER INFORMATION

STORE AT A TEMPERATURE BELOW 110F (43C)

INACTIVE INGREDIENTS

WATER (AQUA), PROPYLENE GLYCOL, PEG-40 HYDROGENATED CASTOR OIL, FRAGRANCE (PARFUM), ACRYLATES/C10-30 ALKYL ACRYLATES CROSSPOLYMER, GLYCERIN, ISOPROPYL MYRISTATE, AMINOMETHYL PROPANOL, TOCOPHERYL ACETATE, MANNITOL, CELLULOSE, HYDROXYPROPYL METHYLCELLULOSE, CHROMIUM HYDROXIDE GREEN (CI 77289), BLUE 1 (CI 42090), YELLOW 10 (CI 47005)